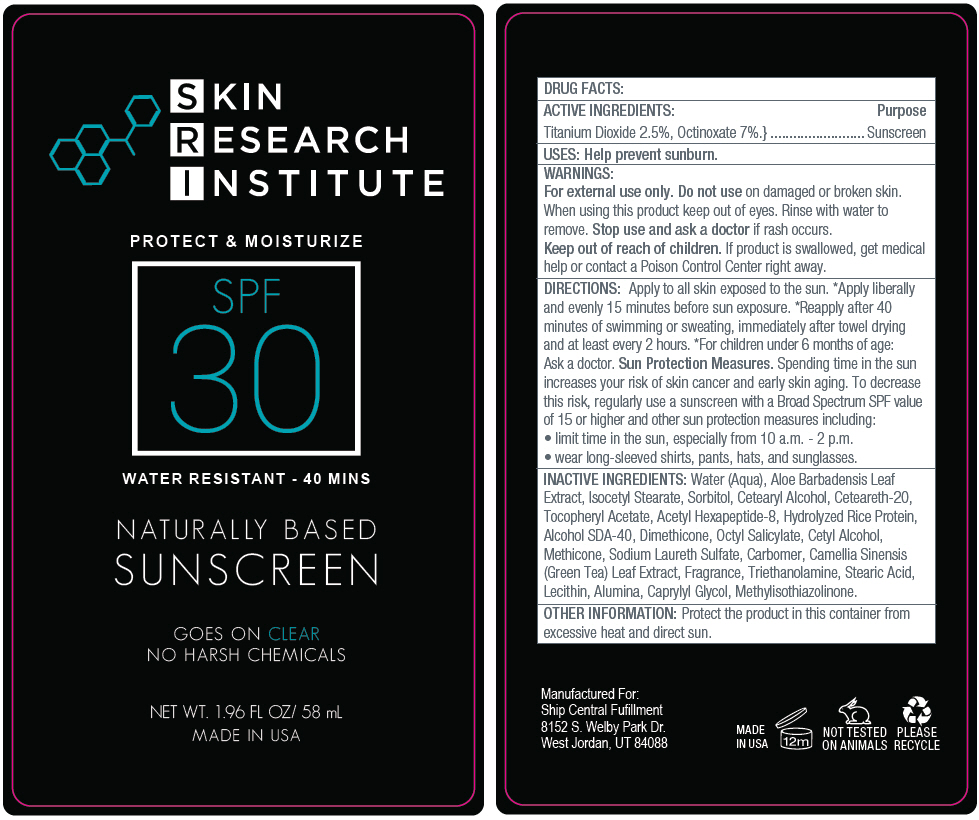 DRUG LABEL: Skin Research Institute Naturally Based Sunscreen SPF 30
NDC: 66163-6504 | Form: LOTION
Manufacturer: Cosmetic Solutions LLC
Category: otc | Type: HUMAN OTC DRUG LABEL
Date: 20190930

ACTIVE INGREDIENTS: OCTINOXATE 70 mg/1 mL; TITANIUM DIOXIDE 25 mg/1 mL
INACTIVE INGREDIENTS: Water; Aloe Vera Leaf; Isocetyl Stearate; Sorbitol; Cetostearyl Alcohol; Polyoxyl 20 Cetostearyl Ether; .Alpha.-Tocopherol Acetate; Acetyl Hexapeptide-8; Dimethicone; Octisalate; Cetyl Alcohol; Methicone (20 Cst); Sodium Laureth-3 Sulfate; Carboxypolymethylene; Green Tea Leaf; Trolamine; Stearic Acid; Triethoxycaprylylsilane; Aluminum Oxide; Caprylyl Glycol; Methylisothiazolinone

Skin Research Institute Naturally Based Sunscreen SPF 30

DRUG FACTS:

ACTIVE INGREDIENTS

Titanium Dioxide 2.5%, Octinoxate 7%.

Purpose

Sunscreen

USES

Help prevent sunburn.

WARNINGS

For external use only. Do not use on damaged or broken skin. When using this product keep out of eyes. Rinse with water to remove. Stop use and ask a doctor if rash occurs.

Keep out of reach of children. If product is swallowed, get medical help or contact a Poison Control Center right away.

DIRECTIONS

Apply to all skin exposed to the sun. *Apply liberally and evenly 15 minutes before sun exposure. *Reapply after 40 minutes of swimming or sweating, immediately after towel drying and at least every 2 hours. *For children under 6 months of age: Ask a doctor. Sun Protection Measures. Spending time in the sun increases your risk of skin cancer and early skin aging. To decrease this risk, regularly use a sunscreen with a Broad Spectrum SPF value of 15 or higher and other sun protection measures including:

- limit time in the sun, especially from 10 a.m. - 2 p.m.
- wear long-sleeved shirts, pants, hats, and sunglasses.

INACTIVE INGREDIENTS

Water (Aqua), Aloe Barbadensis Leaf Extract, Isocetyl Stearate, Sorbitol, Cetearyl Alcohol, Ceteareth-20, Tocopheryl Acetate, Acetyl Hexapeptide-8, Hydrolyzed Rice Protein, Alcohol SDA-40, Dimethicone, Octyl Salicylate, Cetyl Alcohol, Methicone, Sodium Laureth Sulfate, Carbomer, Camellia Sinensis (Green Tea) Leaf Extract, Fragrance, Triethanolamine, Stearic Acid, Lecithin, Alumina, Caprylyl Glycol, Methylisothiazolinone.

OTHER INFORMATION

Protect the product in this container from excessive heat and direct sun.

PRINCIPAL DISPLAY PANEL - 58 mL Tube Label

SKIN
RESEARCH
INSTITUTE

PROTECT & MOISTURIZE

SPF
30

WATER RESISTANT - 40 MINS

NATURALLY BASED
SUNSCREEN

GOES ON CLEAR
NO HARSH CHEMICALS

NET WT. 1.96 FL OZ/ 58 mL
MADE IN USA